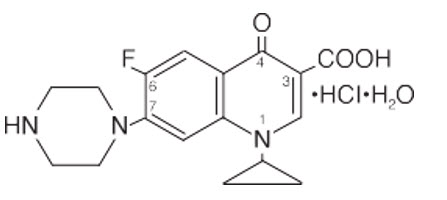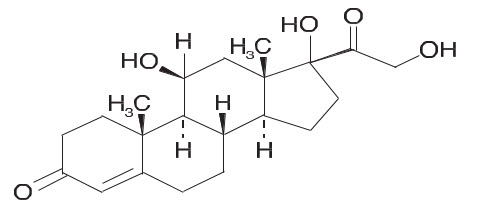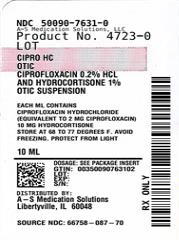 DRUG LABEL: CIPRO HC
NDC: 50090-7631 | Form: SUSPENSION/ DROPS
Manufacturer: A-S Medication Solutions
Category: prescription | Type: HUMAN PRESCRIPTION DRUG LABEL
Date: 20250818

ACTIVE INGREDIENTS: CIPROFLOXACIN HYDROCHLORIDE 2.0 mg/1 mL; HYDROCORTISONE 10 mg/1 mL
INACTIVE INGREDIENTS: POLYVINYL ALCOHOL; SODIUM CHLORIDE; SODIUM ACETATE; ACETIC ACID; POLYSORBATE 20; AQUA; SODIUM HYDROXIDE; HYDROCHLORIC ACID; BENZYL ALCOHOL; HYDROGENATED SOYBEAN PHOSPHATIDYLCHOLINE

CIPRO HC

DESCRIPTION

CIPRO® HC OTIC (ciprofloxacin hydrochloride and hydrocortisone otic suspension) contains the synthetic broad spectrum antibacterial agent, ciprofloxacin hydrochloride, combined with the anti-inflammatory corticosteroid, hydrocortisone, in a preserved, nonsterile suspension for otic use. Each mL of CIPRO® HC OTIC contains ciprofloxacin hydrochloride (equivalent to 2 mg ciprofloxacin), 10 mg hydrocortisone, and 9 mg benzyl alcohol as a preservative. The inactive ingredients are glacial acetic acid, phospholipon 90H (modified lecithin), polysorbate 20, polyvinyl alcohol, purified water, sodium acetate, and sodium chloride. Hydrochloric acid or sodium hydroxide may be added for adjustment of pH.

Ciprofloxacin, a fluoroquinolone, is available as the monohydrochloride monohydrate salt of 1-cyclopropyl-6-fluoro-1,4-dihydro-4-oxo-7-(1-piperazinyl)-3-quinolinecarboxylic acid. Its empirical formula is C17H18FN3O3•HCI•H2O and its chemical structure is as follows:

Hydrocortisone, pregn-4-ene-3, 20-dione, 11, 17, 21-trihydroxy-(11(β)-, is an anti-inflammatory corticosteroid. Its empirical formula is C21H30O5 and its chemical structure is:

CLINICAL PHARMACOLOGY

The plasma concentrations of ciprofloxacin were not measured following three drops of otic suspension administration because the systemic exposure to ciprofloxacin is expected to be below the limit of quantitation of the assay (0.05 μg/mL).

Similarly, the predicted Cmax of hydrocortisone is within the range of endogenous hydrocortisone concentration (0-150 ng/mL), and therefore cannot be differentiated from the endogenous cortisol.

Preclinical studies have shown that CIPRO® HC OTIC was not toxic to the guinea pig cochlea when administered intratympanically twice daily for 30 days and was only weakly irritating to rabbit skin upon repeated exposure.

Hydrocortisone has been added to aid in the resolution of the inflammatory response accompanying bacterial infection.

Microbiology

Ciprofloxacin has in vitro activity against a wide range of gram-positive and gram-negative microorganisms. The bactericidal action of ciprofloxacin results from interference with the enzyme, DNA gyrase, which is needed for the synthesis of bacterial DNA. Cross-resistance has been observed between ciprofloxacin and other fluoroquinolones. There is generally no cross-resistance between ciprofloxacin and other classes of antibacterial agents, such as beta-lactams or aminoglycosides.

Ciprofloxacin has been shown to be active against most strains of the following microorganisms, both in vitro and in clinical infections of acute otitis externa as described in the INDICATIONS AND USAGE section:

Aerobic Gram-positive Microorganism

Staphylococcus aureus

Aerobic Gram-negative Microorganisms

Proteus mirabilis

Pseudomonas aeruginosa

INDICATIONS AND USAGE

CIPRO® HC OTIC is indicated for the treatment of acute otitis externa in adult and pediatric patients, one year and older, due to susceptible strains of Pseudomonas aeruginosa, Staphylococcus aureus, and Proteus mirabilis.

CONTRAINDICATIONS

CIPRO® HC OTIC is contraindicated in persons with a history of hypersensitivity to hydrocortisone, ciprofloxacin, or any member of the quinolone class of antimicrobial agents. This nonsterile product should not be used if the tympanic membrane is known or suspected to be perforated. Use of this product is contraindicated in viral infections of the external canal, including varicella and herpes simplex infections.

WARNINGS

NOT FOR OPHTHALMIC USE. NOT FOR INJECTION.

CIPRO® HC OTIC should be discontinued at the first appearance of a skin rash or any other sign of hypersensitivity. Serious and occasionally fatal hypersensitivity (anaphylactic) reactions, some following the first dose, have been reported in patients receiving systemic quinolones. Serious acute hypersensitivity reactions may require immediate emergency treatment. The dropper cap contains natural rubber (latex) which may cause severe allergic reactions.

PRECAUTIONS

General:

As with other antibiotic preparations, use of this product may result in overgrowth of nonsusceptible organisms, including fungi. If the infection is not improved after one week of therapy, cultures should be obtained to guide further treatment.

Information for Patients:

If rash or allergic reaction occurs, discontinue use immediately and contact your physician.

Do not use in the eyes.

Avoid contaminating the dropper with material from the ear, fingers, or other sources.

Protect from light.

Shake well immediately before using.

Discard unused portion after therapy is completed.

Carcinogenesis, Mutagenesis, Impairment of Fertility:

Eight in vitro mutagenicity tests have been conducted with ciprofloxacin, and the test results are listed below:

Salmonella/Microsome Test (Negative)

E. coli DNA Repair Assay (Negative)

Mouse Lymphoma Cell Forward Mutation Assay (Positive)

Chinese Hamster V79 Cell HGPRT Test (Negative)

Syrian Hamster Embryo Cell Transformation Assay (Negative)

Saccharomyces cerevisiae Point Mutation Assay (Negative)

Saccharomyces cerevisiae Mitotic Crossover and Gene Conversion Assay (Negative)

Rat Hepatocyte DNA Repair Assay (Positive)

Thus, 2 of the 8 tests were positive, but results of the following 3 in vivo test systems gave negative results:

Rat Hepatocyte DNA Repair Assay

Micronucleus Test (Mice)

Dominant Lethal Test (Mice)

Long-term carcinogenicity studies in mice and rats have been completed for ciprofloxacin. After daily oral doses of 750 mg/kg (mice) and 250 mg/kg (rats) were administered for up to 2 years, there was no evidence that ciprofloxacin had any carcinogenic or tumorigenic effects in these species. No long-term studies of CIPRO® HC OTIC suspension have been performed to evaluate carcinogenic potential.

Fertility studies performed in rats at oral doses of ciprofloxacin up to 100 mg/kg/day revealed no evidence of impairment. This would be over 1000 times the maximum recommended clinical dose of ototopical ciprofloxacin based upon body surface area, assuming total absorption of ciprofloxacin from the ear of a patient treated with CIPRO® HC OTIC twice per day.

Long-term studies have not been performed to evaluate the carcinogenic potential or the effect on fertility of topical hydrocortisone. Mutagenicity studies with hydrocortisone were negative.

Pregnancy: Teratogenic Effects:

Reproduction studies have been performed in rats and mice using oral doses of up to 100 mg/kg and IV doses up to 30 mg/kg and have revealed no evidence of harm to the fetus as a result of ciprofloxacin. In rabbits, ciprofloxacin (30 and 100 mg/kg orally) produced gastrointestinal disturbances resulting in maternal weight loss and an increased incidence of abortion, but no teratogenicity was observed at either dose. After intravenous administration of doses up to 20 mg/kg, no maternal toxicity was produced in the rabbit, and no embryotoxicity or teratogenicity was observed.

Corticosteroids are generally teratogenic in laboratory animals when administered systemically at relatively low dosage levels. The more potent corticosteroids have been shown to be teratogenic after dermal application in laboratory animals.

Animal reproduction studies have not been conducted with CIPRO® HC OTIC. No adequate and well-controlled studies have been performed in pregnant women. Caution should be exercised when CIPRO® HC OTIC is used by a pregnant woman.

Nursing Mothers:

Ciprofloxacin is excreted in human milk with systemic use. It is not known whether ciprofloxacin is excreted in human milk following topical otic administration. Because of the potential for serious adverse reactions in nursing infants, a decision should be made whether to discontinue nursing or to discontinue the drug, taking into account the importance of the drug to the mother.

Pediatric Use:

The safety and efficacy of CIPRO® HC OTIC have been established in pediatric patients 2 years and older (131 patients) in adequate and well-controlled clinical trials. Efficacy has been extrapolated for patients, age 1 year and above based on studies in adults and older pediatric patients.

ADVERSE REACTIONS

In Phase 3 clinical trials, a total of 564 patients were treated with CIPRO® HC OTIC. Adverse events with at least remote relationship to treatment included headache (1.2%) and pruritus (0.4%). The following treatment-related adverse events were each reported in a single patient: migraine, hypesthesia, paresthesia, fungal dermatitis, cough, rash, urticaria, and alopecia.

The following reactions have been identified during post-approval use of CIPRO® HC OTIC in clinical practice. Because they are reported voluntarily from a population of unknown size, estimates of frequency cannot be made. The reactions, which have been chosen for inclusion due to either their seriousness, frequency of reporting, possible causal connection to CIPRO® HC OTIC, or a combination of these factors, include: dizziness, ear canal erythema, ear congestion, hypoacusis, and medication residue.

DOSAGE AND ADMINISTRATION

SHAKE WELL IMMEDIATELY BEFORE USING.

For children (age 1 year and older) and adults, 3 drops of the suspension should be instilled into the affected ear twice daily for seven days. The suspension should be warmed by holding the bottle in the hand for 1-2 minutes to avoid the dizziness, which may result from the instillation of a cold solution into the ear canal. The patient should lie with the affected ear upward and then the drops should be instilled. This position should be maintained for 30-60 seconds to facilitate penetration of the drops into the ear. Repeat, if necessary, for the opposite ear. Discard unused portion after therapy is completed.

HOW SUPPLIED

Product: 50090-7631

NDC: 50090-7631-0 10 mL in a BOTTLE / 1 in a CARTON